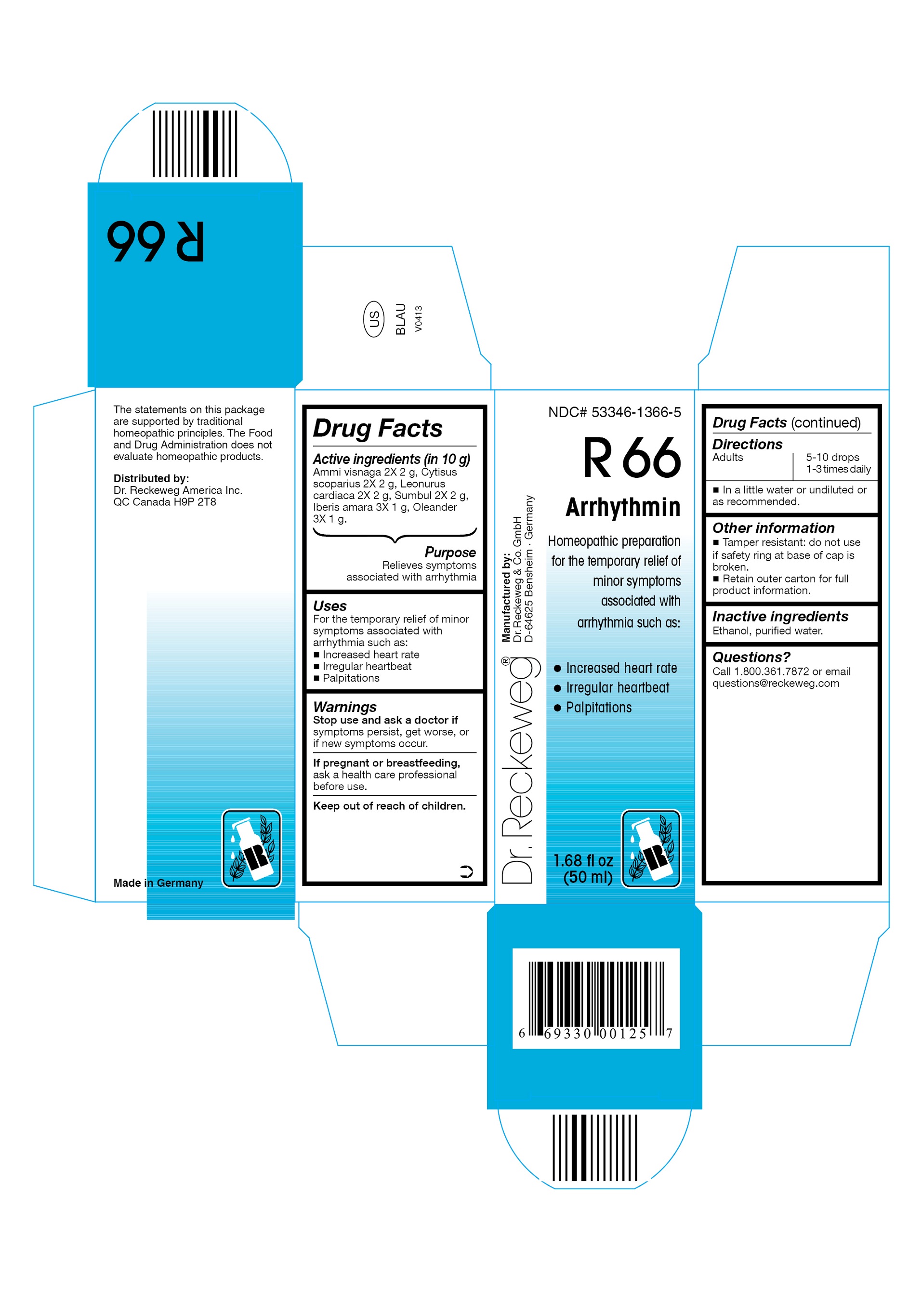 DRUG LABEL: DR. RECKEWEG R66 Arrhythmin
NDC: 53346-1366 | Form: LIQUID
Manufacturer: PHARMAZEUTISCHE FABRIK DR. RECKEWEG & CO
Category: homeopathic | Type: HUMAN OTC DRUG LABEL
Date: 20130404

ACTIVE INGREDIENTS: AMMI VISNAGA FRUIT 2 [hp_X]/50 mL; CYTISUS SCOPARIUS FLOWERING TOP 2 [hp_X]/50 mL; LEONURUS CARDIACA 2 [hp_X]/50 mL; FERULA SUMBUL ROOT 2 [hp_X]/50 mL; IBERIS AMARA SEED 3 [hp_X]/50 mL; NERIUM OLEANDER LEAF 3 [hp_X]/50 mL
INACTIVE INGREDIENTS: ALCOHOL; WATER

DR. RECKEWEG R66 Arrhythmin

Active ingredients

Ammi visnaga 2X 2 g, Cytisus scoparius 2X 2 g, Leonurus cardiaca 2X 2 g, Sumbul 2X 2 g, Iberis amara 3X 1 g, Oleander 3X 1 g in 10 g.

Purpose

Relieves symptoms associated with arrhythmia

Uses

For the temporary relief of minor symptoms associated with arrhythmia such as:

- Increased heart rate
- Irregular heartbeat
- Palpitations

Warnings

Stop use and ask a doctor if symptoms persist, get worse, or if new symptoms occur.

PREGNANCY OR BREAST FEEDING

If pregnant or breastfeeding, ask a health care professional before use.

Keep out of reach of children.

Directions

Adults 5-10 drops 1-3 times daily in a little water or undiluted or as recommended.

Other information

- Tamper resistant: do not use if safety ring at base of cap is broken.
- Retain outer carton for full product information.

Inactive ingredients
Ethanol, purified water.

Questions?

Call 1-800-361-7872 or email questions@reckeweg.com

PACKAGE LABEL

NDC# 53346-1366-5

Dr. Reckeweg R66 Arrhythmin

Homeopathic preparation for the temporary relief of minor symptoms associated with arrhythmia such as:

- Increased heart rate
- Irregular heartbeat
- Palpitations

Manufactured by:

Dr. Reckeweg Co. GmbH

D-64625 Bensheim

Germany

1.68 fl oz
(50 ml)